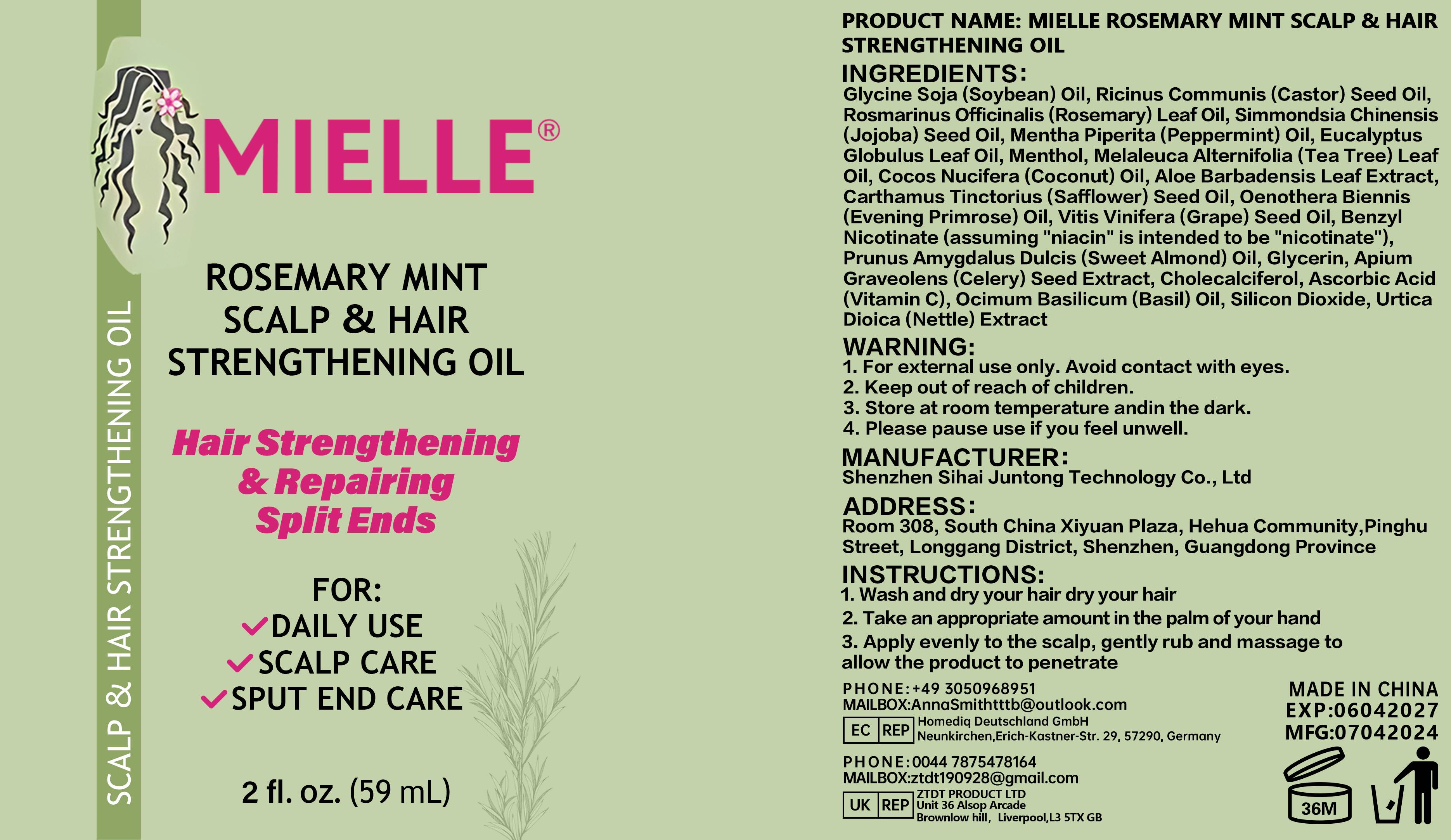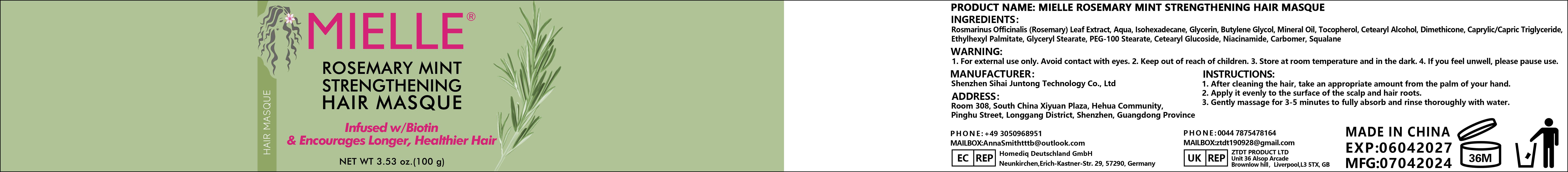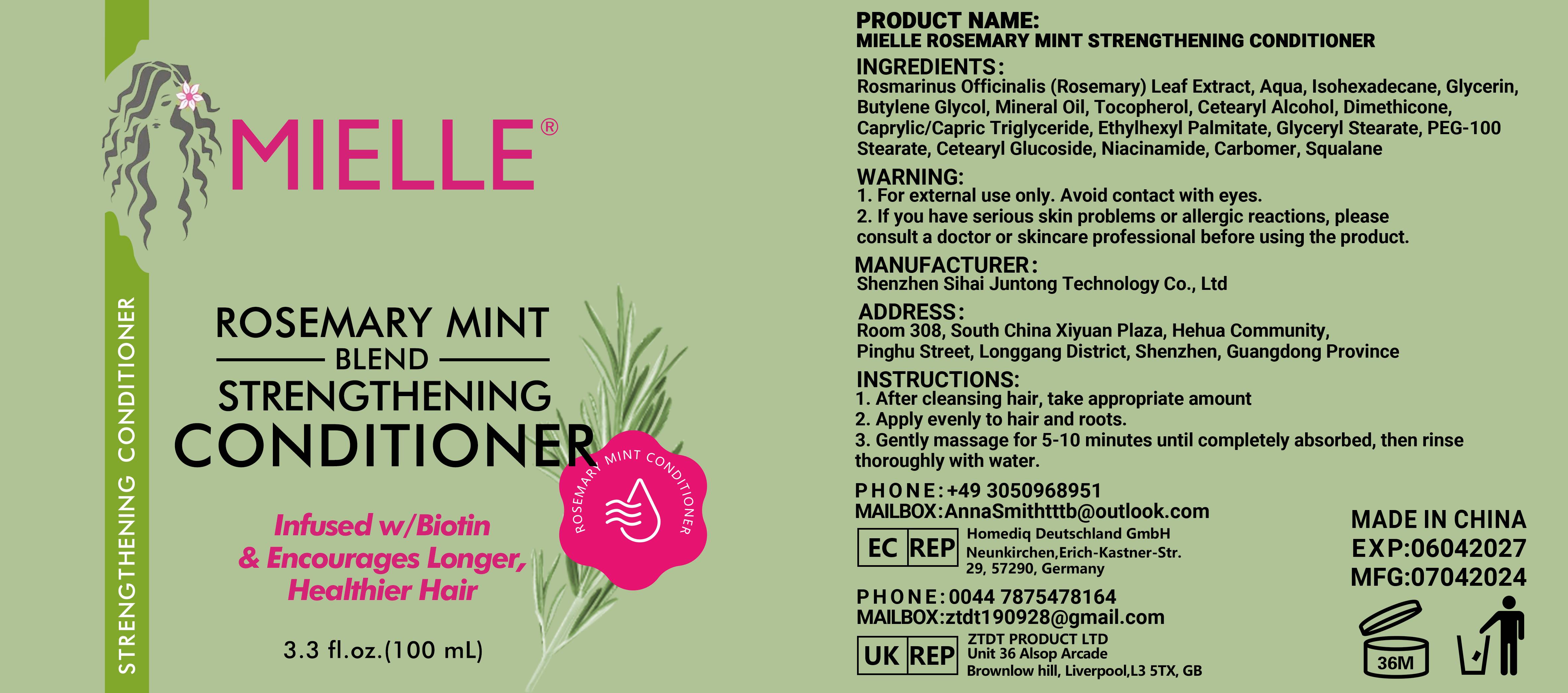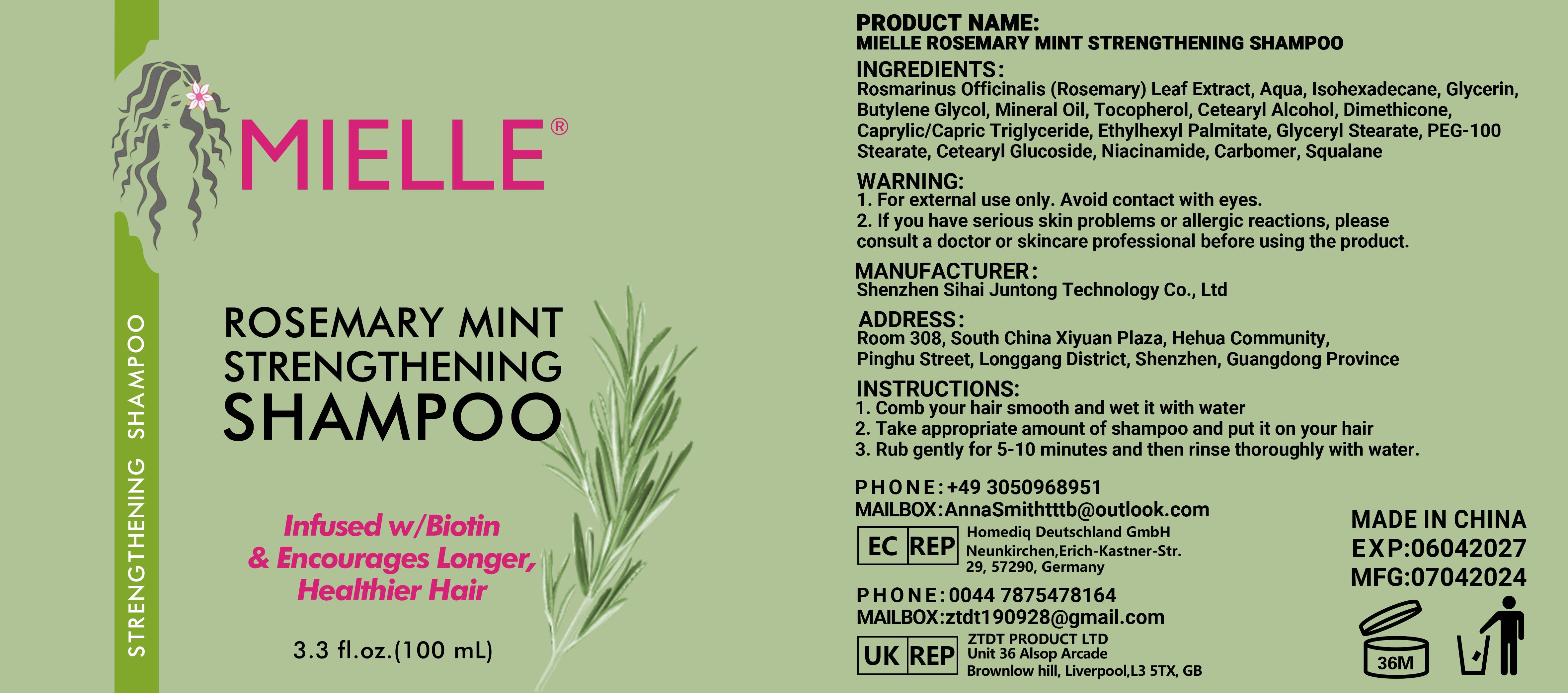 DRUG LABEL: MlELLERosemaryMintShampooConditionerHairMaskOil
NDC: 84350-009 | Form: CREAM
Manufacturer: Shenzhen Sihai Juntong Technology Co., Ltd
Category: otc | Type: HUMAN OTC DRUG LABEL
Date: 20240920

ACTIVE INGREDIENTS: SQUALANE 1 g/100 mg
INACTIVE INGREDIENTS: WATER

ACTIVE INGREDIENT

Rosmarinus Officinalis (Rosemary) Leaf Extract 5%

INACTIVE INGREDIENT

Water 5%

PURPOSE

Moisturizing

WARNINGS

1. For external use only Avoid contact with eves.2. lf you have serous skin problems or alleric reactions, pleaseconsult a
doctor or skincare professional before using the product.

If you have allergic reactions, stop to use

Keep out of reach of children

INDICATIONS AND USAGE

1. After cleansing hair, take appropriate amount2. Apply evenly to hair and roots.3. Gently massage for 5-10 minutes until completely absorbed, then rinsethoroughly with water.

DOSAGE AND ADMINISTRATION

appropriate amount

PACKAGE LABEL

100g NDC:84350-009-01 100ml NDC:84350-009-01 100ml 84350-009-01 59ml NDC：84350-009-01